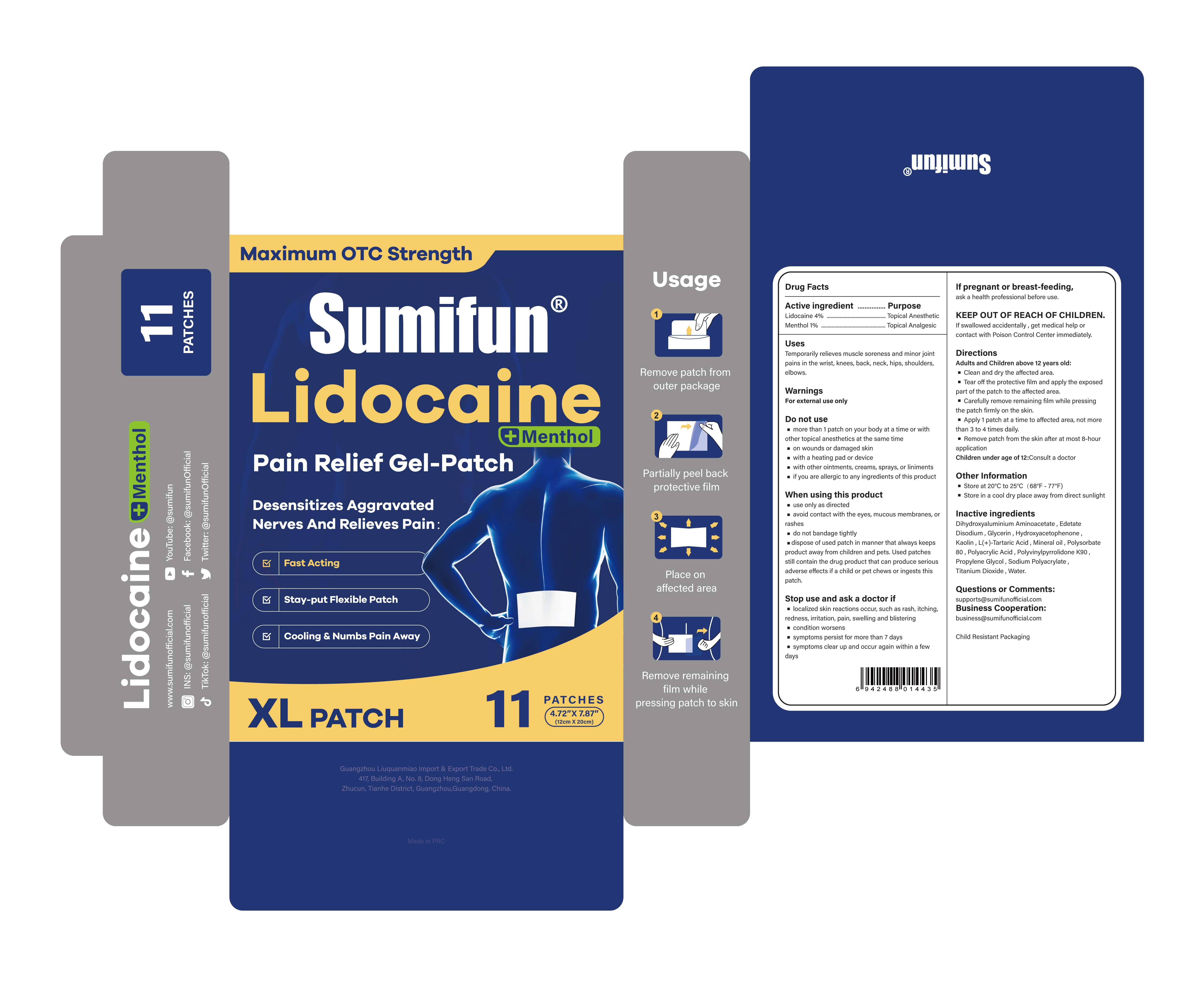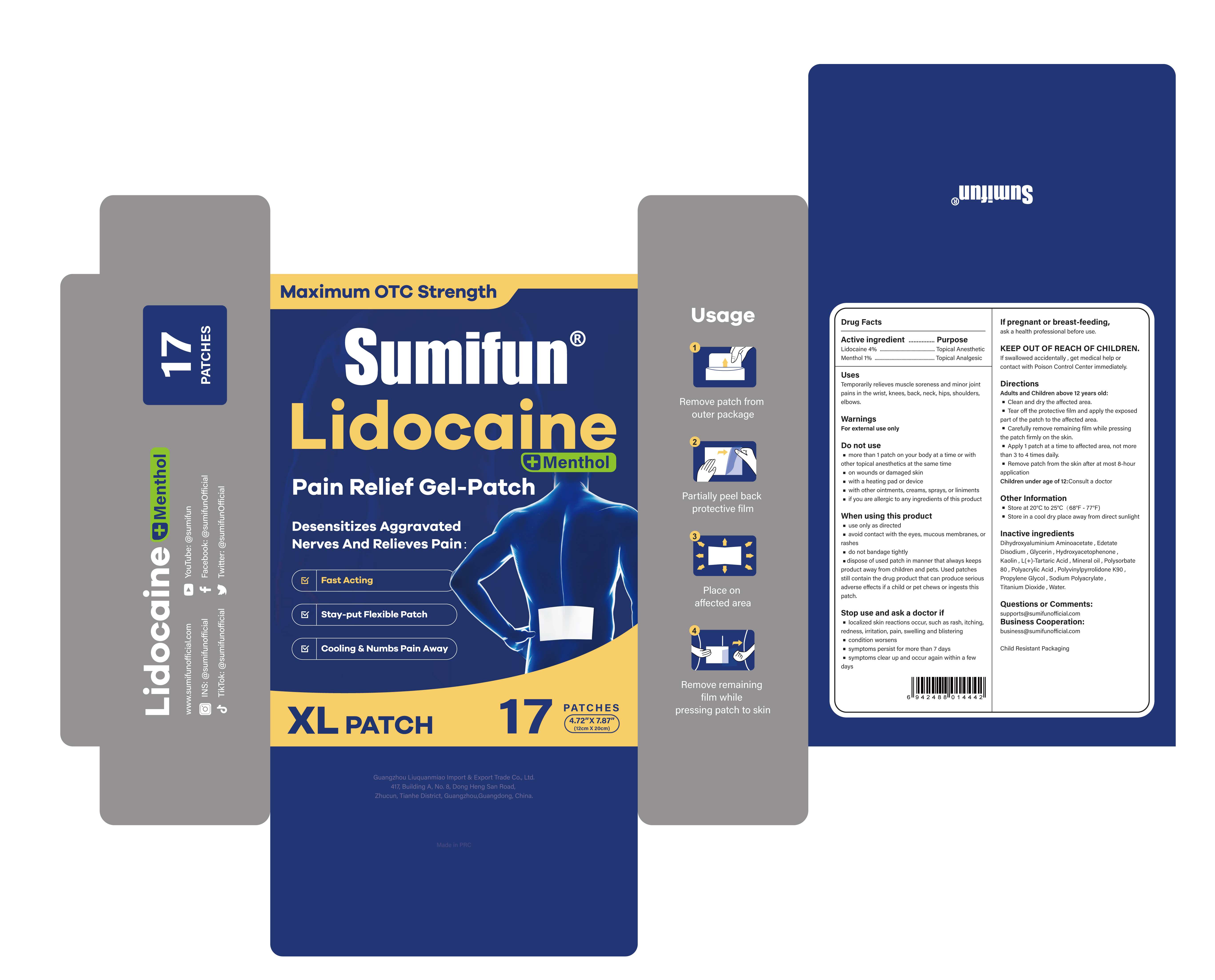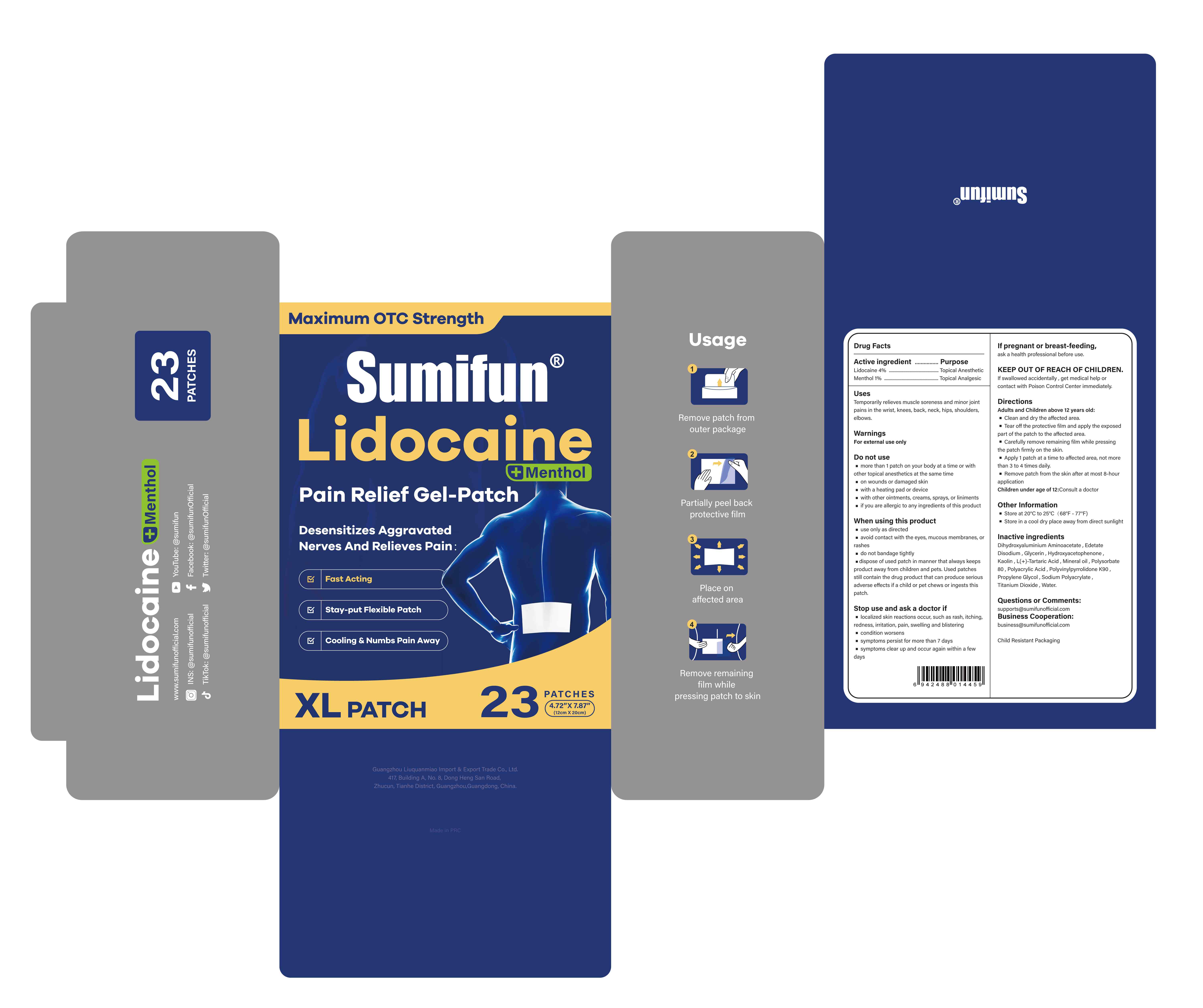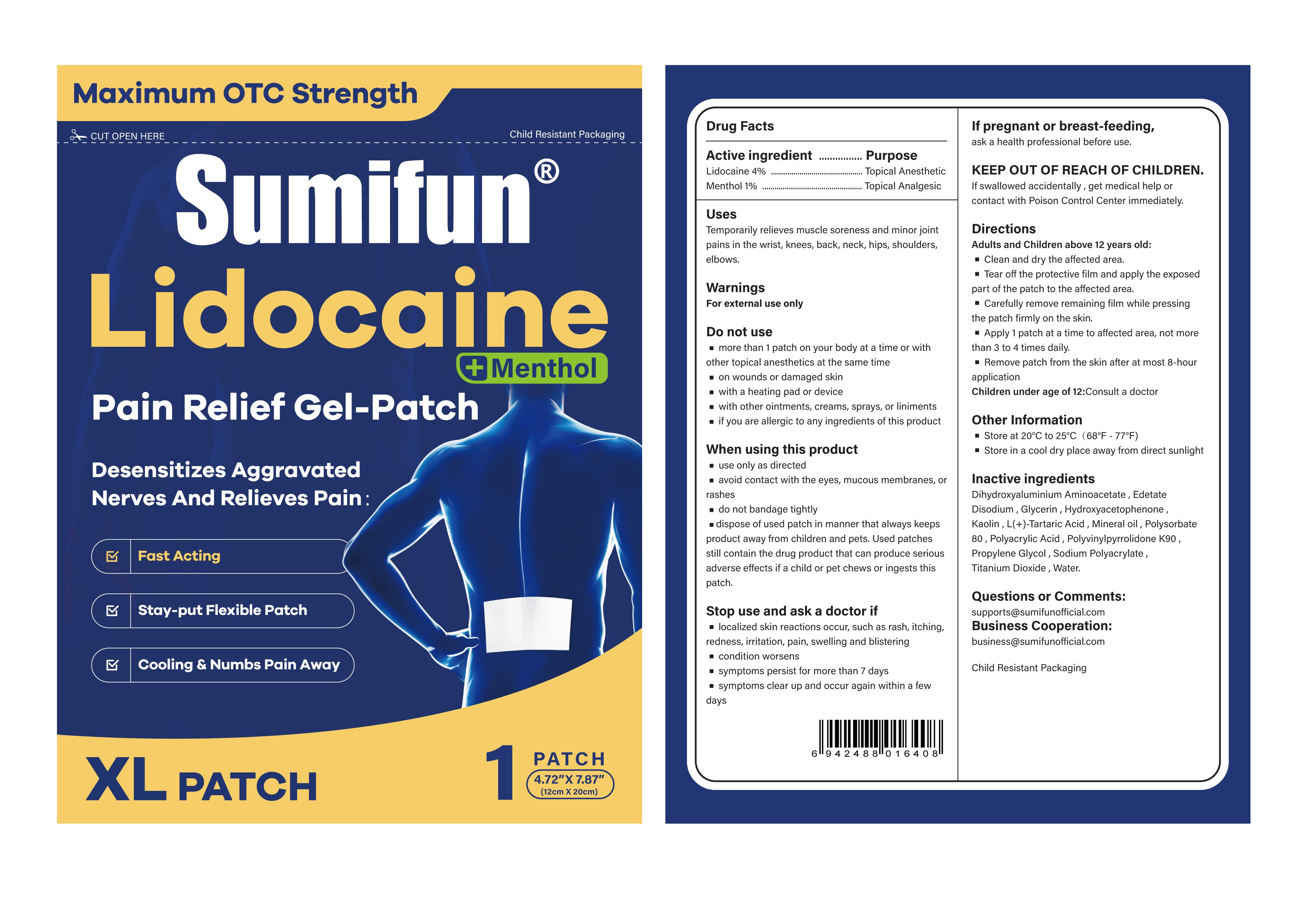 DRUG LABEL: Lidocaine Pain Relief Gel-Patch
NDC: 83602-175 | Form: PATCH
Manufacturer: Guangzhou Liuquanmiao Import & Export Trade Co., Ltd.
Category: otc | Type: HUMAN OTC DRUG LABEL
Date: 20260131

ACTIVE INGREDIENTS: MENTHOL 0.01 g/1 g; LIDOCAINE 0.04 g/1 g
INACTIVE INGREDIENTS: KAOLIN; TARTARIC ACID; WATER; DIHYDROXYALUMINUM AMINOACETATE ANHYDROUS; PROPYLENE GLYCOL; POLYACRYLIC ACID (250000 MW); SODIUM POLYACRYLATE (2500000 MW); TITANIUM DIOXIDE; MINERAL OIL; POLYSORBATE 80; GLYCERIN; EDETATE DISODIUM; POVIDONE K90; HYDROXYACETOPHENONE

Lidocaine Pain Relief Gel-Patch

Active Ingredient

Lidocaine 4% w/w ...... Purpose: Topical anesthetic

Menthol 1% w/w ...... Purpose: Topical analgesic

Purposes

Topical anesthetic (Lidocaine)

Topical analgesic (Menthol)

Uses

Temporarily relieves muscle soreness and minor joint pains in the wrist, knees, neck, shoulders, elbows.

Warnings

For external use only

When using this product:

- use only as directed
- avoid contact with the eyes, mucous membranes or rashes
- do not bandage tightly
- dispose of used patch in manner that always keeps product away from children and pets. Used patches still contain the drug product that can produce serious adverse effects if a child or pet chews or ingests this patch.

Do not use:

- more than 1 patch on your body at a time or with other topical anesthetics at the same time
- on wounds or damaged skin
- with a heating pad or device
- with other ointments, creams, sprays, or liniments
- If you are allergic to any ingredients of this product

Stop use and ask a doctor if:

- localized skin reactions occur, such as rash, itching, redness, irritation, pain, swelling and blistering
- condition worsen
- symptoms persist for more than 7 days
- symptoms clear up and occur again within a few days

If pregnant or breast-feeding,

Ask a health professional before use

Keep out of reach of children.

If swallowed, get medical help or contact a Poison Control Center immediately.

Directions

Adult and Children above12 years old:

- Clean and dry the affected area
- Tear off the protective film and apply the exposed part of the patch to the affected area.
- Carefully remove remaining film while pressing the patch firmly on the skin.
- Apply 1 patch at a time to affected area, not morethan 3 to 4 times daily.
- Remove patch from the skin after at most 8-hour application

Children under 12 years of age:Consult a doctor

Other Information

· Store at 20°C to 25°C（68°F - 77°F)

· Store in a cool dry place away from direct sunlight

Inactive Ingredients

Dihydroxyaluminium Aminoacetate, Edetate Disodium, Glycerin, Hydroxyacetophenone,Kaolin, L(+)-Tartaric Acid, Mineral oil, Polysorbate80, Polyacrylic Acid , Polyvinylpyrrolidone K90,Propylene Glycol, Sodium Polyacrylate,

Titanium Dioxide, Water.

Questions or Comments

supports@sumifunofficialcom